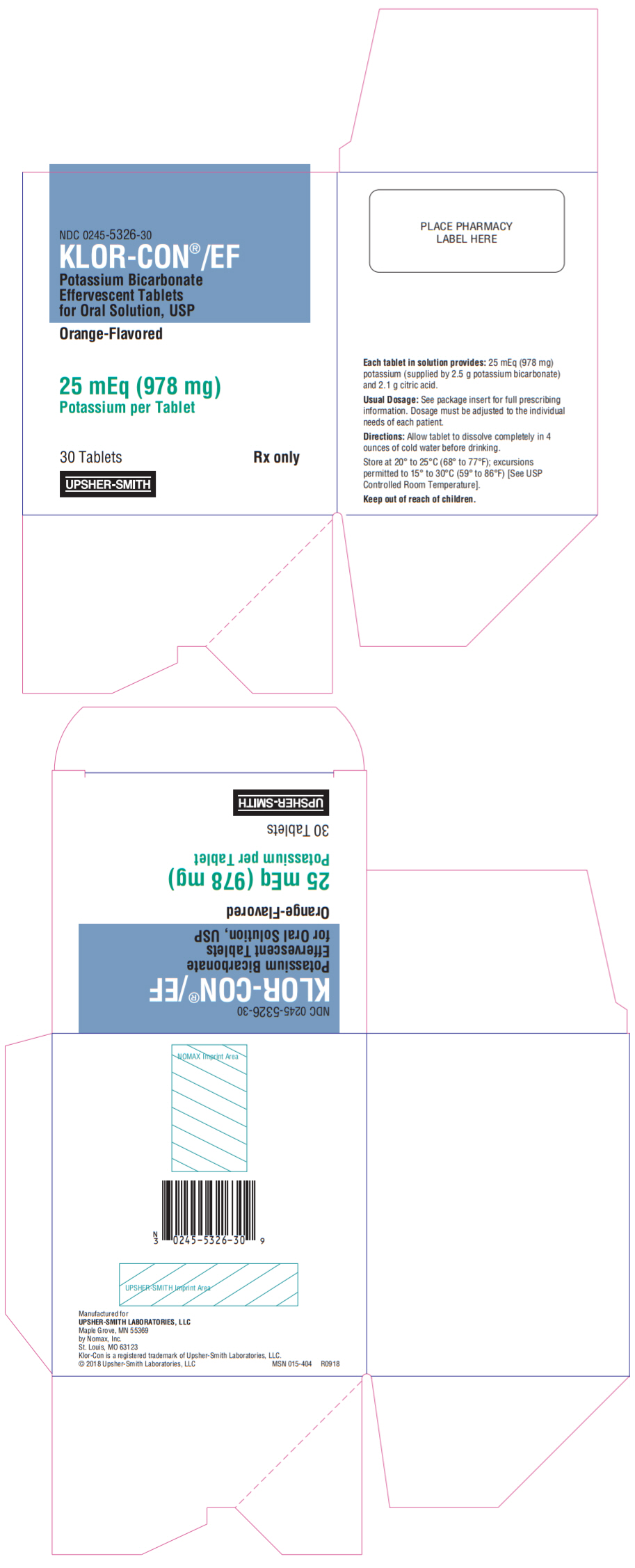 DRUG LABEL: KLOR-Con/EF
NDC: 0245-5326 | Form: TABLET, EFFERVESCENT
Manufacturer: Upsher-Smith Laboratories, Inc.
Category: prescription | Type: HUMAN PRESCRIPTION DRUG LABEL
Date: 20250714

ACTIVE INGREDIENTS: POTASSIUM BICARBONATE 978 mg/1 1
INACTIVE INGREDIENTS: FD&C YELLOW NO. 6; MICROCRYSTALLINE CELLULOSE; MINERAL OIL; SACCHARIN; TALC

KLOR-CON®/EF
Potassium Bicarbonate Effervescent Tablets for Oral Solution, USP

Rx only

DESCRIPTION

Orange-flavored KLOR-CON®/EF (potassium bicarbonate effervescent tablets for oral solution, USP) are an oral potassium supplement offered as effervescent tablets in individual packets for dissolution in water. Each tablet contains potassium bicarbonate 2.5 g and citric acid 2.1 g which in solution provides 25 mEq (978 mg) potassium as bicarbonate and citrate. Also contains: FD&C Yellow No. 6, FD&C Yellow No. 6 Lake, microcrystalline cellulose, mineral oil, orange flavor, saccharin and talc. KLOR-CON®/EF tablets are sugar-free.

CLINICAL PHARMACOLOGY

The potassium ion is the principal intracellular cation of most body tissues. Potassium ions participate in a number of essential physiological processes, including the maintenance of intracellular tonicity, the transmission of nerve impulses, the contraction of cardiac, skeletal and smooth muscle and the maintenance of normal renal function.

The intracellular concentration of potassium is approximately 150 to 160 mEq per liter. The normal adult plasma concentration is 3.5 to 5 mEq per liter. An active ion transport system maintains this gradient across the plasma membrane.

Potassium is a normal dietary constituent and under steady state conditions the amount of potassium absorbed from the gastrointestinal tract is equal to the amount excreted in the urine. The usual dietary intake of potassium is 50 to 100 mEq per day.

Potassium depletion will occur whenever the rate of potassium loss through renal excretion and/or loss from the gastrointestinal tract exceeds the rate of potassium intake. Such depletion usually develops as a consequence of therapy with diuretics, primary or secondary hyperaldosteronism, diabetic ketoacidosis or inadequate replacement of potassium in patients on prolonged parenteral nutrition. Depletion can develop rapidly with severe diarrhea, especially if associated with vomiting. Potassium depletion due to these causes is usually accompanied by a concomitant loss of chloride and is manifested by hypokalemia and metabolic alkalosis. Potassium depletion may produce weakness, fatigue, disturbances of cardiac rhythm (primarily ectopic beats), prominent U-waves in the electrocardiogram and, in advanced cases, flaccid paralysis and/or impaired ability to concentrate urine.

If potassium depletion associated with metabolic alkalosis cannot be managed by correcting the fundamental cause of the deficiency (e.g., patients require long-term diuretic therapy), supplemental potassium in the form of high potassium food or potassium salts may be able to restore normal potassium levels.

In rare circumstances (e.g., patients with renal tubular acidosis), potassium depletion may be associated with metabolic acidosis and hyperchloremia. In such patients, potassium replacement should be accomplished with potassium salts such as potassium bicarbonate, potassium citrate, potassium acetate or potassium gluconate.

INDICATIONS AND USAGE

1. For the treatment of patients with hypokalemia, with or without metabolic alkalosis; in digitalis intoxication; and in patients with hypokalemic familial periodic paralysis. If hypokalemia is the result of diuretic therapy, consideration should be given to the use of a lower dose of diuretic, which may be sufficient without leading to hypokalemia.
2. For the prevention of hypokalemia in patients who would be at particular risk if hypokalemia were to develop (e.g., digitalized patients or patients with significant cardiac arrhythmias).

The use of potassium salts in patients receiving diuretics for uncomplicated essential hypertension is often unnecessary when such patients have a normal dietary pattern and when low doses of the diuretic are used. Serum potassium should be checked periodically, however, and if hypokalemia occurs, dietary supplementation with potassium-containing foods may be adequate to control milder cases. In more severe cases, and if dose adjustment of the diuretic is ineffective or unwarranted, supplementation with potassium salts may be indicated.

CONTRAINDICATIONS

Potassium supplements are contraindicated in patients with hyperkalemia since a further increase in serum potassium concentration in such patients can produce cardiac arrest. Hyperkalemia may complicate any of the following conditions: chronic renal failure, systemic acidosis such as diabetic acidosis, acute dehydration, extensive tissue breakdown as in severe burns, adrenal insufficiency or the administration of a potassium-sparing diuretic (e.g., spironolactone, triamterene or amiloride) [see OVERDOSAGE] .

WARNINGS

Hyperkalemia

[see OVERDOSAGE]

In patients with impaired mechanisms for excreting potassium, the administration of potassium salts can produce hyperkalemia and cardiac arrest. This occurs most commonly in patients given potassium by the intravenous route but may also occur in patients given potassium orally. Potentially fatal hyperkalemia can develop rapidly and be asymptomatic. The use of potassium salts in patients with chronic renal disease, or any other condition which impairs potassium excretion, requires particularly careful monitoring of the serum potassium concentration and appropriate dosage adjustment.

Interaction with Potassium-Sparing Diuretics

Hypokalemia should not be treated by the concomitant administration of potassium salts and a potassium-sparing diuretic (e.g., spironolactone, triamterene or amiloride), since the simultaneous administration of these agents can produce severe hyperkalemia.

Interaction with Angiotensin Converting Enzyme Inhibitors

Angiotensin converting enzyme (ACE) inhibitors (e.g., captopril, enalapril) will produce some potassium retention by inhibiting aldosterone production. Potassium supplements should be given to patients receiving ACE inhibitors only with close monitoring.

Metabolic Acidosis

Hypokalemia in patients with metabolic acidosis should be treated with an alkalinizing potassium salt such as potassium bicarbonate, potassium citrate, potassium acetate or potassium gluconate.

PRECAUTIONS

General

The diagnosis of potassium depletion is ordinarily made by demonstrating hypokalemia in a patient with a clinical history suggesting some cause for potassium depletion. In interpreting the serum potassium level, the physician should be aware that acute alkalosis per secan produce hypokalemia in the absence of a deficit in total body potassium while acute acidosis per secan increase the serum potassium concentration into the normal range even in the presence of a reduced total body potassium. The treatment of potassium depletion, particularly in the presence of cardiac disease, renal disease or acidosis, requires careful attention to acid-base balance and appropriate monitoring of serum electrolytes, the electrocardiogram and the clinical status of the patient.

Information for Patients

Remind the patient to take this medicine following the frequency and amount prescribed. This is especially important if the patient is also taking diuretics and/or digitalis preparations.

Laboratory Tests

When blood is drawn for analysis of plasma potassium, artifactual elevations can occur after improper venipuncture technique or as a result of in vitrohemolysis of the sample.

Drug Interactions

Potassium-sparing diuretics, angiotensin converting enzyme inhibitors [see WARNINGS] .

Carcinogenesis, Mutagenesis, Impairment of Fertility

Carcinogenicity, mutagenicity and fertility studies in animals have not been performed. Potassium is a normal dietary constituent.

Pregnancy

Animal reproduction studies have not been conducted with potassium salts. It is not known if potassium salts cause fetal harm when administered to a pregnant woman or affect reproductive capacity. Potassium supplements should be given to a pregnant woman only if clearly needed.

Nursing Mothers

Many drugs are excreted in human milk and because of the potential for serious adverse reactions in nursing infants from oral potassium supplements, a decision should be made whether to discontinue nursing or discontinue the drug, considering the importance of the drug to the mother.

Pediatric Use

Safety and effectiveness in children have not been established.

ADVERSE REACTIONS

One of the most severe adverse effects is hyperkalemia [see CONTRAINDICATIONS, WARNINGSand OVERDOSAGE] .

The most common adverse reactions to oral potassium salts are nausea, vomiting, flatulence, abdominal pain/discomfort and diarrhea. These symptoms are due to irritation of the gastrointestinal tract and are best managed by diluting the preparation further, taking the dose with meals or reducing the dose.

OVERDOSAGE

The administration of oral potassium salts to persons with normal excretory mechanisms for potassium rarely causes serious hyperkalemia. However, if excretory mechanisms are impaired or if potassium is administered too rapidly intravenously, potentially fatal hyperkalemia can result [see CONTRAINDICATIONSand WARNINGS] . It is important to recognize that hyperkalemia is usually asymptomatic and may be manifested only by an increased serum potassium concentration (6.5 to 8.0 mEq/L) and characteristic electrocardiographic changes (peaking of T-waves, loss of P-wave, depression of S-T segment and prolongation of the QT interval). Late manifestations include muscle paralysis and cardiovascular collapse from cardiac arrest (9 to 12 mEq/L).

Treatment measures for hyperkalemia include the following: 1) elimination of foods and medications containing potassium and elimination of potassium-sparing diuretics; 2) intravenous administration of 300 to 500 mL/hr of 10% dextrose solution containing 10 to 20 units of crystalline insulin per 1,000 mL; 3) correction of acidosis, if present, with intravenous sodium bicarbonate; 4) use of exchange resins, hemodialysis or peritoneal dialysis.

In treating hyperkalemia in patients who have been stabilized on digitalis, too rapid a lowering of the serum potassium concentration can produce digitalis toxicity.

DOSAGE AND ADMINISTRATION

The usual dietary potassium intake by the average adult is 50 to 100 mEq per day. Potassium depletion sufficient to cause hypokalemia usually requires the loss of 200 mEq or more of potassium from the total body store.

Dosage must be adjusted to the individual needs of each patient. The dose for the prevention of hypokalemia is typically 25 mEq per day. Doses of 50 to 100 mEq per day or more are used for the treatment of potassium depletion. Dosage should be divided if more than 25 mEq per day is given such that no more than 25 mEq is given in a single dose.

The usual adult dose is 25 to 100 mEq of potassium per day (one KLOR-CON®/EF tablet 1 to 4 times daily after meals).

Each KLOR-CON®/EF tablet should be dissolved in at least 4 ounces of cold or ice water. These preparations, like other potassium supplements, must be properly diluted to avoid the possibility of gastrointestinal irritation.

HOW SUPPLIED

KLOR-CON®/EF Potassium Bicarbonate Effervescent Tablets for Oral Solution, USP are supplied as follows:

- Cartons of 30 individually wrapped tablets NDC 0245-5326-30
- Cartons of 100 individually wrapped tablets NDC 0245-5326-01

STORAGE AND HANDLING

Store at 20° to 25°C (68° to 77°F); excursions permitted to 15° to 30°C (59° to 86°F) [See USP Controlled Room Temperature].

Manufactured for
UPSHER-SMITH LABORATORIES, LLC
Maple Grove, MN 55369
by Nomax, Inc.
St. Louis, MO 63123

Klor-Con is a registered trademark of Upsher-Smith Laboratories, LLC.

Revised: 6/2020

PRINCIPAL DISPLAY PANEL - 978 mg Tablet Pouch Carton

NDC 0245-5326-30

KLOR-CON®/EF

Potassium Bicarbonate
Effervescent Tablets
for Oral Solution, USP

Orange-Flavored

25 mEq (978 mg)
Potassium per Tablet

30 Tablets
Rx only

UPSHER-SMITH